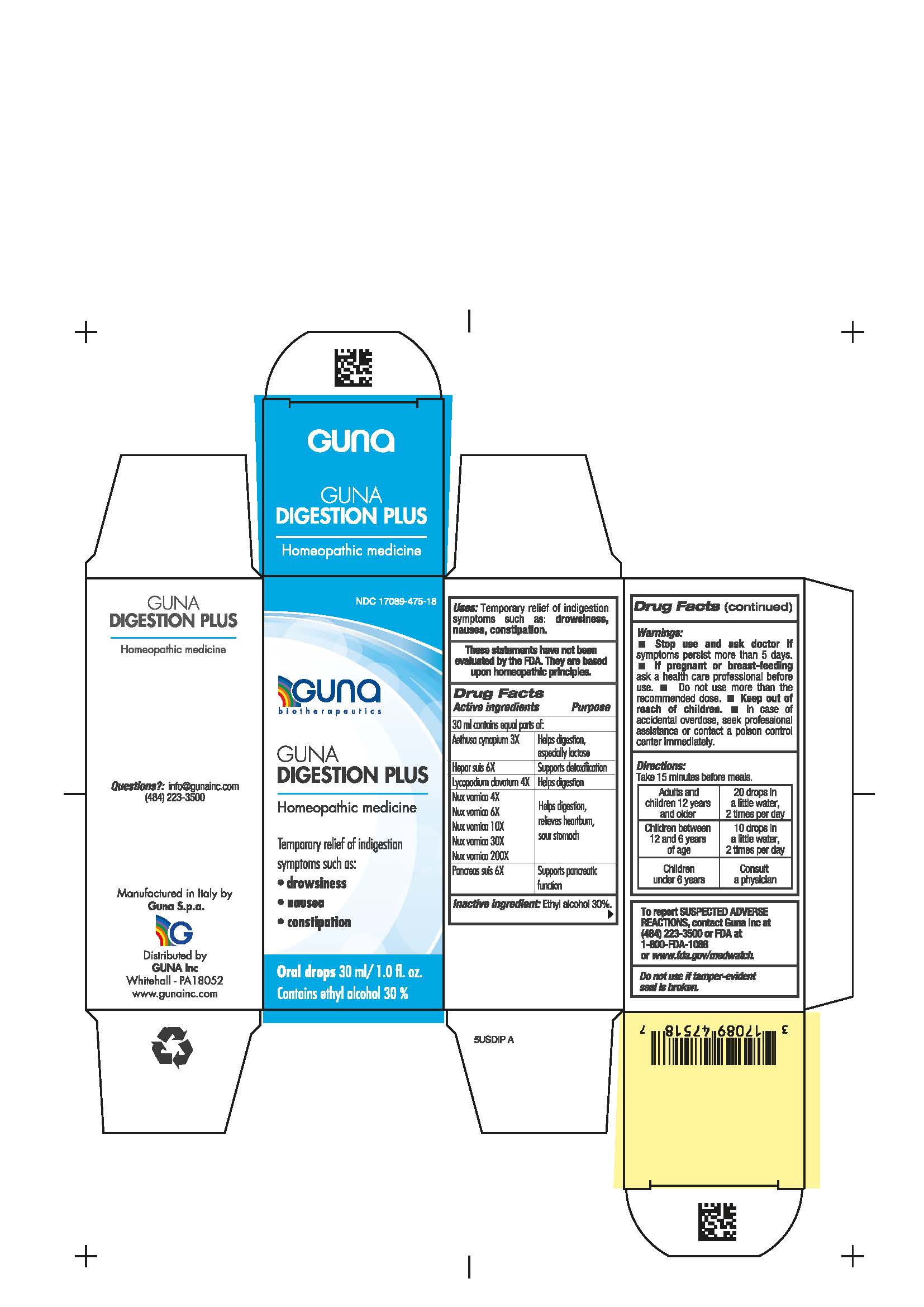 DRUG LABEL: GUNA DIGESTION PLUS
NDC: 17089-475 | Form: SOLUTION/ DROPS
Manufacturer: Guna spa
Category: homeopathic | Type: HUMAN OTC DRUG LABEL
Date: 20210217

ACTIVE INGREDIENTS: PORK LIVER 6 [hp_X]/30 mL; LYCOPODIUM CLAVATUM SPORE 4 [hp_X]/30 mL; SUS SCROFA PANCREAS 6 [hp_X]/30 mL; AETHUSA CYNAPIUM 3 [hp_X]/30 mL; STRYCHNOS NUX-VOMICA SEED 4 [hp_X]/30 mL
INACTIVE INGREDIENTS: ALCOHOL 9 mL/30 mL

GUNA DIGESTION PLUS

INDICATIONS AND USAGE

Take 15 minutes before meals

Inactive ingredient: Ethyl alcohol 30%.

QUESTIONS

Questions?: info@gunainc.com
Tel. (484) 223-3500

DIRECTIONS

Take 15 minutes before meals.
Adults and children 12 years and older 20 drops in a little water, 2 times per day
Children between 12 and 6 years of age 10 drops in a little water, 2 times per day .
Children under 6 years consult a physician

WARNINGS

Keep out of reach of children

PREGNANCY

If pregnant or breast-feeding ask a health care professional before use

WARNINGS

Stop use and ask doctor if symptoms persist more than 5 days.
If pregnant or breast-feeding ask a health care professional before use.
Do not use more than the recommended dose.

Keep out of reach of children.

In case of overdose, seek professional assistance or contact a Poison Control Center right away.
Contains ethyl alcohol 30%

USES

Temporary relief of indigestion symptoms such as:

- drowsiness
- nausea
- constipation

ACTIVE INGREDIENTS/PURPOSE

Aethusa cynapium 3X Helps digestion, especially lactose

Hepar suis 6X Supports detoxification

Lycopodium clavatum 4X Helps digestion

Nux vomica 4X, 6X, 10X, 30X, 200X Helps digestion, relieves heartburn, sour stomach

Pancreas suis 6X Supports pancreatic function